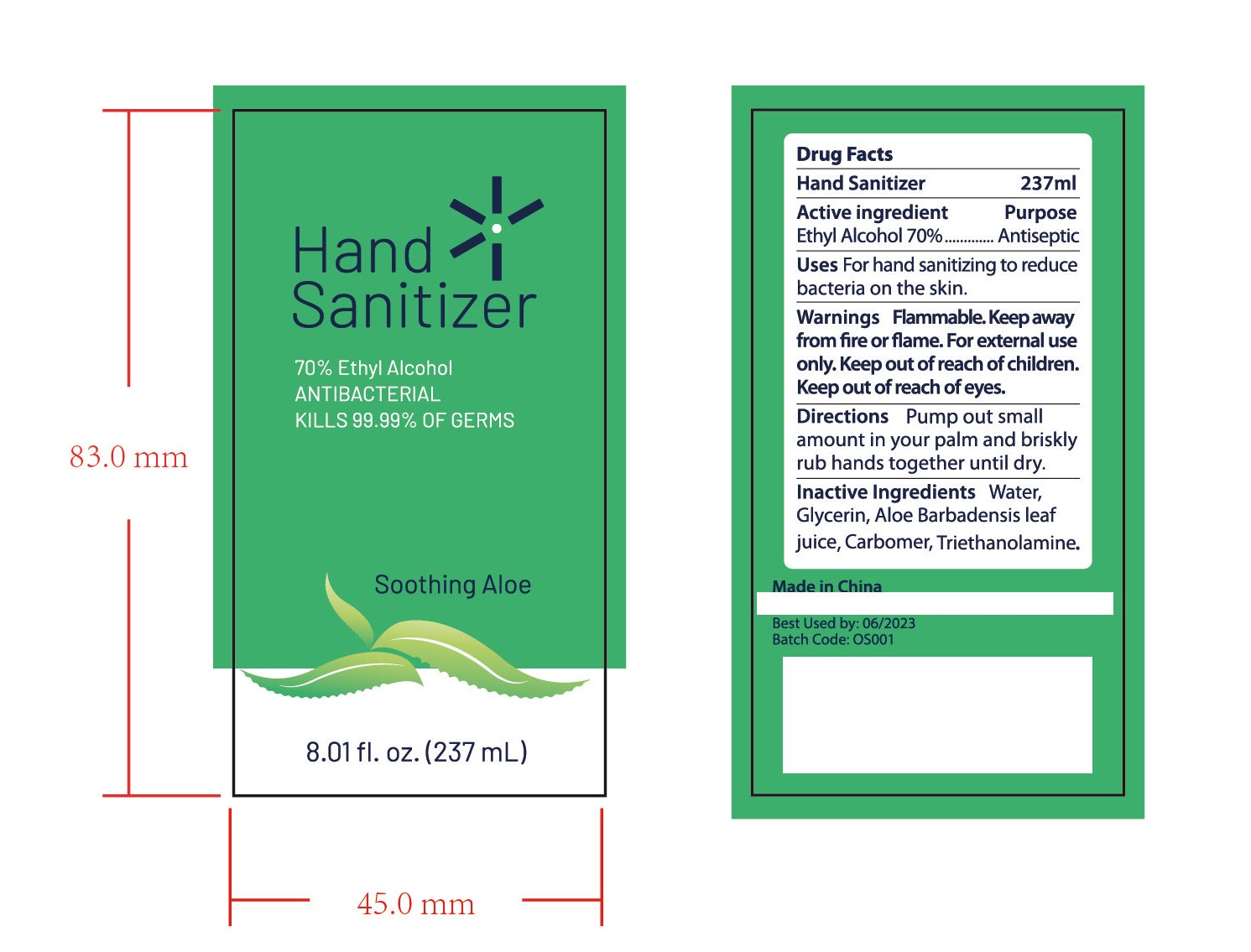 DRUG LABEL: HAND SANITIZER
NDC: 47993-271 | Form: GEL
Manufacturer: NINGBO JIANGBEI OCEAN STAR TRADING CO.,LTD
Category: otc | Type: HUMAN OTC DRUG LABEL
Date: 20201105

ACTIVE INGREDIENTS: ALCOHOL 70 g/112 mL
INACTIVE INGREDIENTS: GLYCERIN; TRIETHANOLAMINE BENZOATE; ALOE VERA LEAF; WATER; CARBOMER 940

47993-271

Active ingredients

Ethyl Alcohol 70%

PURPOSE

Antiseptic

Uses：

For hand sanitizing to reduce bacteria on the skin.

Warnings:

Flammable. Keep away from fire or flame. For external use only. Keep out of reach of children. Keep out of reach of eyes.

Keep out of reach of children.

Directions:

Pump out small amount in your palm and briskly rub hands together until dry.

Inactive Ingredients:

Water,Glycerin,Aloe Barbadensis leaf juice,Carbomer,Triethanolamine